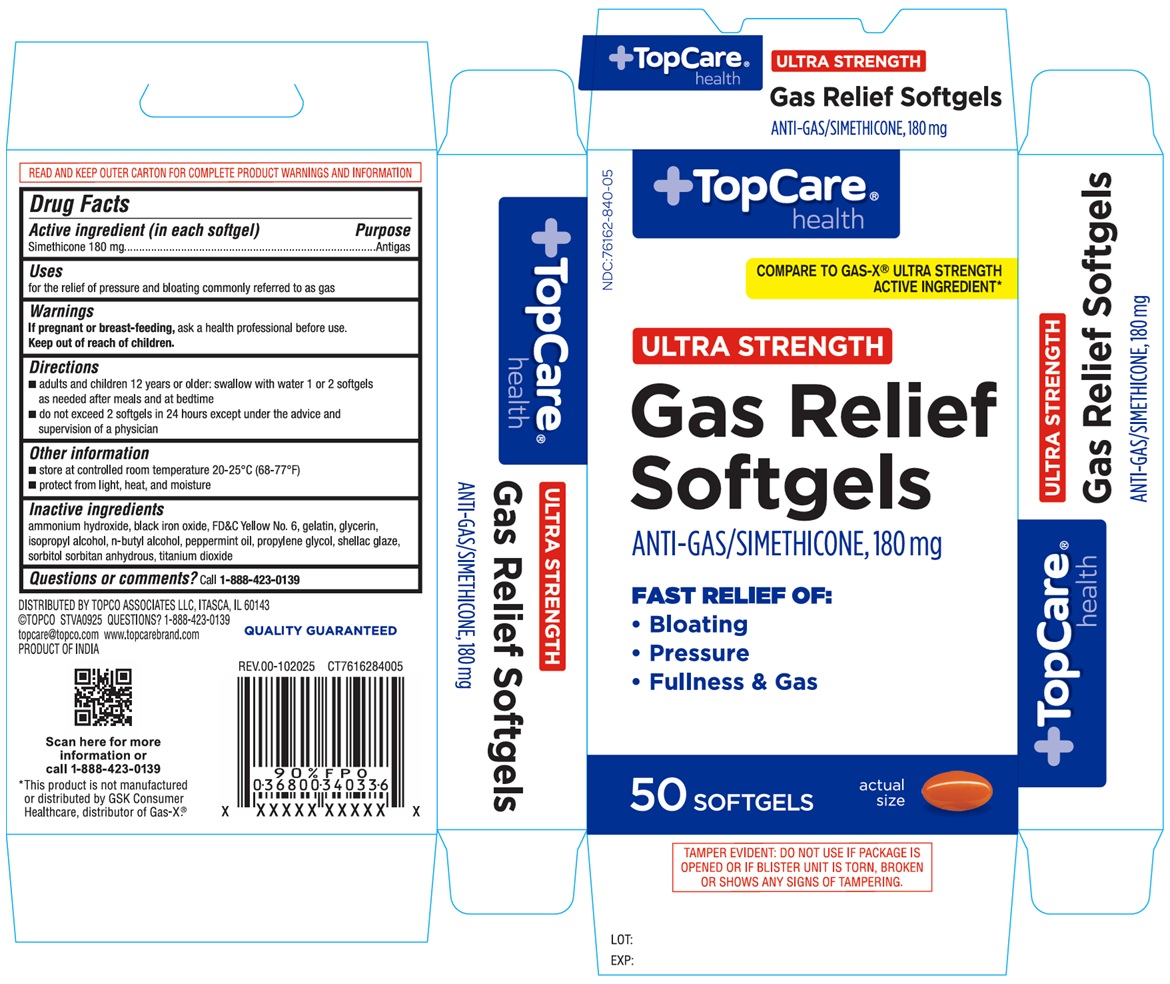 DRUG LABEL: ULTRA STRENGTH Gas Relief Softgels
NDC: 76162-840 | Form: CAPSULE, LIQUID FILLED
Manufacturer: Topco Associates LLC
Category: otc | Type: HUMAN OTC DRUG LABEL
Date: 20251213

ACTIVE INGREDIENTS: DIMETHICONE, UNSPECIFIED 180 mg/1 1
INACTIVE INGREDIENTS: AMMONIA; FERROSOFERRIC OXIDE; FD&C YELLOW NO. 6; GELATIN, UNSPECIFIED; GLYCERIN; ISOPROPYL ALCOHOL; BUTYL ALCOHOL; PEPPERMINT OIL; PROPYLENE GLYCOL; SHELLAC; SORBITOL; SORBITAN; TITANIUM DIOXIDE

TopCare® health ULTRA STRENGTH Gas Relief Softgels

Active ingredient (in each softgel)

Simethicone 180 mg

Purpose

Antigas

Uses

for the relief of pressure and bloating commonly referred to as gas

Warnings

If pregnant or breast-feeding, ask a health professional before use.

Keep out of reach of children.

Directions

• adults and children 12 years or older: swallow with water 1 or 2 softgels as needed after meals and at bedtime
• do not exceed 2 softgels in 24 hours except under the advice and supervision of a physician

Other information

• store at controlled room temperature 20-25°C (68-77°F)
• protect from light, heat, and moisture

Inactive ingredients

ammonium hydroxide, black iron oxide, FD&C Yellow No. 6, gelatin, glycerin, isopropyl alcohol, n-butyl alcohol, peppermint oil, propylene glycol, shellac glaze, sorbitol sorbitan anhydrous, titanium dioxide

Questions or comments?

Call 1-888-423-0139

COMPARE TO GAS-X® ULTRA STRENGTH ACTIVE INGREDIENT*

FAST RELIEF OF:
• Bloating
• Pressure
• Fullness & Gas

READ AND KEEP OUTER CARTON FOR COMPLETE PRODUCT WARNINGS AND INFORMATION

DISTRIBUTED BY TOPCO ASSOCIATES LLC, ITASCA, IL 60143
©TOPCO STVA0925
topcare@topco.com www.topcarebrand.com
PRODUCT OF INDIA

QUALITY GUARANTEED

*This product is not manufactured or distributed by GSK Consumer Healthcare, distributor of Gas-X®.

TAMPER EVIDENT: DO NOT USE IF PACKAGE IS OPENED OR IF BLISTER UNIT IS TORN, BROKEN OR SHOWS ANY SIGNS OF TAMPERING.